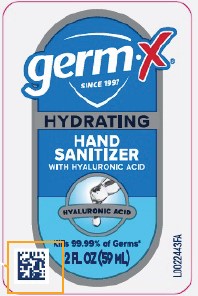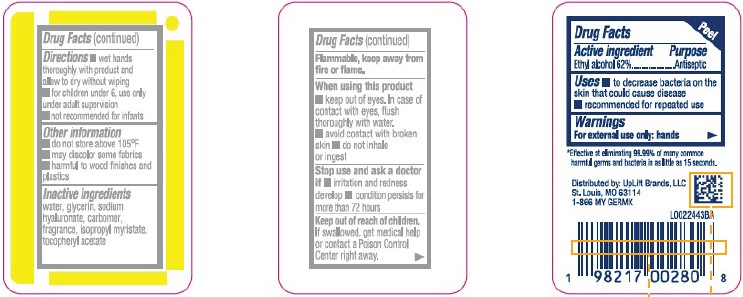 DRUG LABEL: Ethyl Alcohol
NDC: 83986-969 | Form: GEL
Manufacturer: UpLift Brands, LLC
Category: otc | Type: HUMAN OTC DRUG LABEL
Date: 20251205

ACTIVE INGREDIENTS: ALCOHOL 62 mL/100 mL
INACTIVE INGREDIENTS: HYALURONATE SODIUM; GLYCERIN; ISOPROPYL MYRISTATE; WATER; CARBOMER HOMOPOLYMER, UNSPECIFIED TYPE; .ALPHA.-TOCOPHEROL ACETATE

Germ-X D69.001/D69AA
Germ-X Hydrating Hand Sanitizer & Hyaluronic Acid

Active ingredient

Ethyl alcohol 62%

Purpose

Antiseptic

Uses

- to decrease bacteria on the skin that could cause disease
- recommended for repeated use

Warnings

For external use only: hands

Flammable, keep away from fire or flame.

When using this product

- keep out of eyes. In case of contact with eyes, flush thoroughly with water.
- avoid contact with broken skin
- do not inhale or ingest

Stop use and ask a doctor if

- irritation and redness develop
- condition persists for more than 72 hours

Keep out of reach of children.

If swallowed, get medical help or contact a Poison Control Center right away.

Directions

- wet hands thoroughly with product and allow to dry without wiping
- for children under 6, use only under adult supervision
- not recommended for infants

Other information

- do not store above 105⁰F
- may discolor some fabrics
- harmful to wood finishes and plastics

Inactive ingredients

water, glycerin, sodium hyaluronate, carbomer, fragrance, isopropyl myristate, tocopheryl acetate

Adverse Reaction

Distributed by:

UpLift Brands, LLC, St. Louis, MO 63114

1-866 MY GERMX

Claims

*Effective at eliminating 99.99% of many common harmful germs and bacteria in as little as 15 seconds.

PRINCIPAL DISPLAY PANEL

germ X®

SINCE 1997

HYDRATING

HAND SANITIZER

WITH HYALURONIC ACID

HYALURONIC ACID

KILLS 99.99% OF GERMS*

2 FL OZ (59 mL)